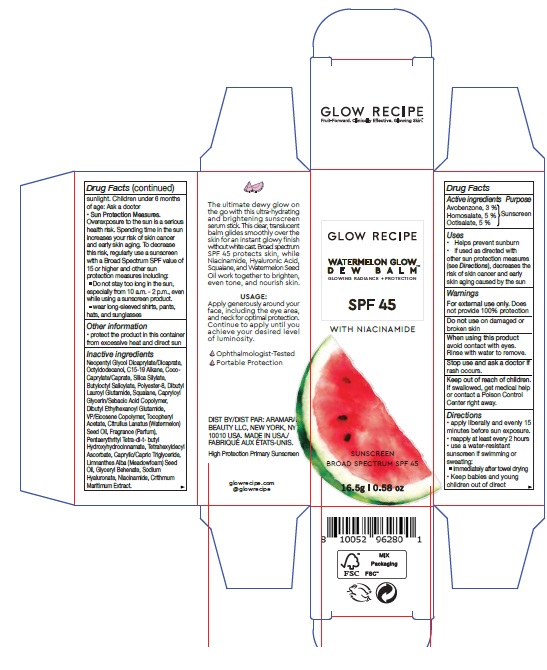 DRUG LABEL: GLOW RECIPE WATERMELON GLOW DEW BALM SPF 45
NDC: 72156-003 | Form: STICK
Manufacturer: Aramara Beauty LLC dba Glow Recipe
Category: otc | Type: HUMAN OTC DRUG LABEL
Date: 20241017

ACTIVE INGREDIENTS: OCTISALATE 50 mg/1 g; HOMOSALATE 50 mg/1 g; AVOBENZONE 30 mg/1 g
INACTIVE INGREDIENTS: POLYESTER-8 (1400 MW, CYANODIPHENYLPROPENOYL CAPPED); BUTYLOCTYL SALICYLATE; GLYCERYL MONOBEHENATE; CAPRYLOYL GLYCERIN/SEBACIC ACID COPOLYMER (2000 MPA.S); WATERMELON SEED OIL; TETRAHEXYLDECYL ASCORBATE; DIBUTYL LAUROYL GLUTAMIDE; SQUALANE; EICOSYL POVIDONE; MEADOWFOAM SEED OIL; NEOPENTYL GLYCOL DICAPRYLATE/DICAPRATE; OCTYLDODECANOL; NIACINAMIDE; CRITHMUM MARITIMUM; COCO-CAPRYLATE/CAPRATE; MEDIUM-CHAIN TRIGLYCERIDES; HYALURONATE SODIUM; .ALPHA.-TOCOPHEROL ACETATE, D-; DIBUTYL ETHYLHEXANOYL GLUTAMIDE; PENTAERYTHRITOL TETRAKIS(3-(3,5-DI-TERT-BUTYL-4-HYDROXYPHENYL)PROPIONATE); C15-19 ALKANE

GLOW RECIPE WATERMELON GLOW DEW BALM SPF 45

Active ingredients

Avobenzone, 3 %
Homosalate, 5 %
Octisalate, 5 %

Purpose

Sunscreen

Uses

- Helps prevent sunburn
- if used as directed with other sun protection measures (see Directions), decreases the risk of skin cancer and early skin aging caused by the sun

Warnings

For external use only. Does not provide 100% protection

Do not use

on damaged or broken skin

When using this product

avoid contact with eyes. Rinse with water to remove.

Stop use and ask a doctor if

rash occurs.

Keep out of reach of children.

If swallowed, get medical help or contact a Poison Control Center right away.

Directions

- apply liberally and evenly 15 minutes before sun exposure.
- reapply at least every 2 hours
- use a water-resistant sunscreen if swimming or sweating: immediately after towel drying
- Keep babies and young children out of direct sunlight. Children under 6 months of age: Ask a doctor
- Sun Protection Measures. Overexposure to the sun is a serious health risk. Spending time in the sun increases your risk of skin cancer and early skin aging. To decrease this risk, regularly use a sunscreen with a Broad Spectrum SPF value of 15 or higher and other sun protection measures including:
- Do not stay too long in the sun, especially from 10 a.m. - 2 p.m., even while using a sunscreen product.
- wear long-sleeved shirts, pants, hats, and sunglasses

Other information

- protect the product in this container from excessive heat and direct sun

Inactive ingredients

Neopentyl Glycol Dicaprylate/Dicaprate, Octyldodecanol, C15-19 Alkane, Coco-Caprylate/Caprate, Silica Silylate,Butyloctyl Salicylate, Polyester-8, Dibutyl Lauroyl Glutamide, Squalane, Capryloyl Glycerin/Sebacic Acid Copolymer, Dibutyl Ethylhexanoyl Glutamide, VP/Eicosene Copolymer, Tocopheryl Acetate, Citrullus Lanatus (Watermelon) Seed Oil, Fragrance (Parfum), Pentaerythrityl Tetra-di-t- butyl Hydroxyhydrocinnamate, Tetrahexyldecyl Ascorbate, Caprylic/Capric Triglyceride, Limnanthes Alba (Meadowfoam) Seed Oil, Glyceryl Behenate, Sodium Hyaluronate, Niacinamide, Crithmum Maritimum Extract.